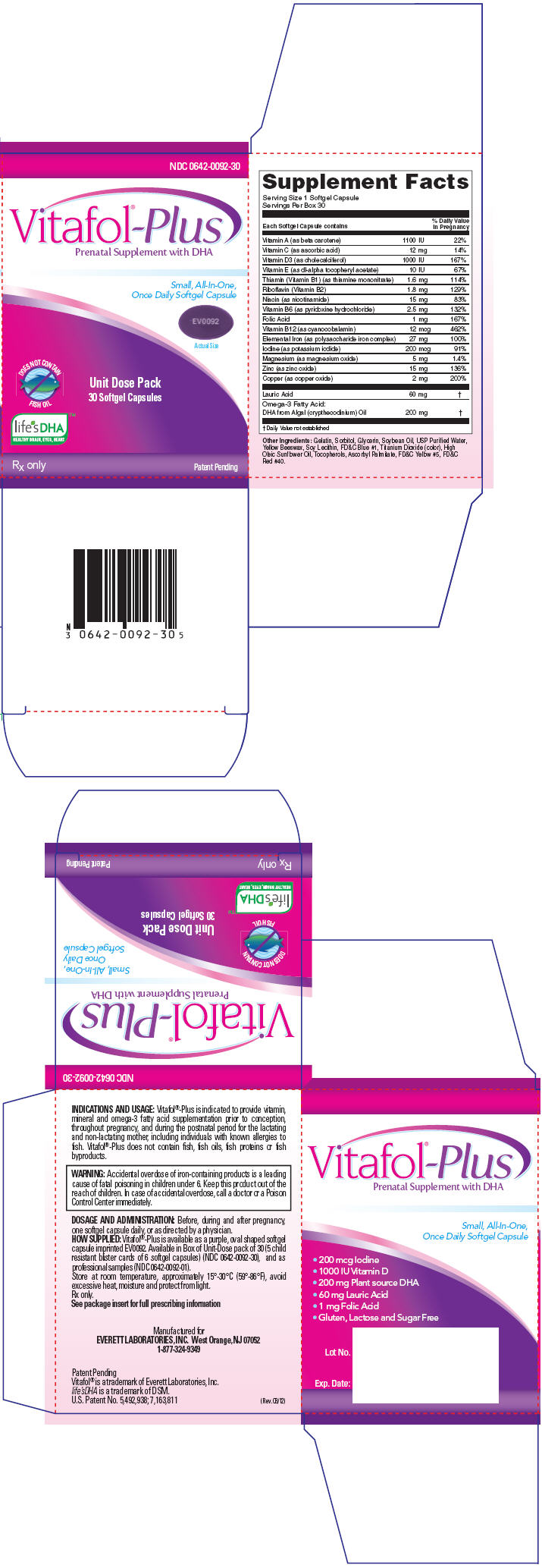 DRUG LABEL: Vitafol 
NDC: 0642-0092 | Form: CAPSULE, LIQUID FILLED
Manufacturer: Everett Laboratories, Inc.
Category: prescription | Type: HUMAN PRESCRIPTION DRUG LABEL
Date: 20120418

ACTIVE INGREDIENTS: Omega-3 Fatty Acids 200 mg/1 1; Niacin 15 mg/1 1; .Alpha.-Tocopherol 10 [iU]/1 1; Vitamin D 1000 [iU]/1 1; Lauric Acid 60 mg/1 1; Vitamin A 1100 [iU]/1 1; Ascorbic Acid 12 mg/1 1; Thiamine Mononitrate 1.6 mg/1 1; Riboflavin 1.8 mg/1 1; Pyridoxine Hydrochloride 2.5 mg/1 1; Cyanocobalamin 12 ug/1 1; Iron 27 mg/1 1; Zinc 15 mg/1 1; Copper 2 mg/1 1; Iodine 200 ug/1 1; Magnesium 5 mg/1 1; Folic Acid 1 mg/1 1
INACTIVE INGREDIENTS: Gelatin; Sorbitol; Glycerin; Water; Yellow Wax; Soybean Oil; Lecithin, Soybean; Titanium Dioxide; FD&C Yellow No. 5; FD&C Red No. 40; FD&C Blue No. 1; Sunflower Oil; Tocopherol; Ascorbyl Palmitate

Vitafol®-Plus
Prenatal Supplement with DHA

Rx only

DESCRIPTION

Composition

Each Softgel Capsule Contains:

Vitamins and Minerals:
Vitamin A (as beta carotene) | 1100 IU
Vitamin C (as ascorbic acid) | 12 mg
Vitamin D3 (as cholecalciferol) | 1000 IU
Vitamin E (as dl-alpha tocopheryl acetate) | 10 IU
Thiamin (Vitamin B1) (as thiamine mononitrate) | 1.6 mg
Riboflavin (Vitamin B2) | 1.8 mg
Niacin (as nicotinamide) | 15 mg
Vitamin B6 (as pyridoxine hydrochloride) | 2.5 mg
Folic Acid | 1 mg
Vitamin B12 (as cyanocobalamin) | 12 mcg
Elemental Iron (as polysaccharide iron complex) | 27mg
Iodine (as potassium iodide) | 200 mcg
Magnesium (as magnesium oxide) | 5 mg
Zinc (as zinc oxide) | 15 mg
Copper (as copper oxide) | 2 mg
Lauric Acid | 60 mg
Omega-3 FATTY ACID
DHA from Algal (crypthecodinium) Oil | 200 mg

Other Ingredients

Gelatin, Sorbitol, Glycerin, Soybean Oil, USP Purified Water, Yellow Beeswax, Soy Lecithin, FD&C Blue #1, Titanium Dioxide (color), High Oleic Sunflower Oil, Tocopherols, Ascorbyl Palmitate, FD&C Yellow #5, FD&C Red #40.

INDICATIONS AND USAGE

Vitafol®-Plus is indicated to provide vitamin, mineral and omega-3 fatty acid supplementation prior to conception, throughout pregnancy, and during the postnatal period for the lactating and non-lactating mother, including individuals with known allergies to fish. Vitafol®-Plus does not contain fish, fish oils, fish proteins or fish byproducts.

CONTRAINDICATIONS

Vitafol®-Plus is contraindicated in patients with hypersensitivity to any of its components or color additives.

Folic acid is contraindicated in patients with untreated and uncomplicated pernicious anemia, and in those with anaphylactic sensitivity to folic acid.

Iron therapy is contraindicated in patients with hemochromatosis and patients with iron storage disease or the potential for iron storage disease due to chronic hemolytic anemia (e.g., inherited anomalies of hemoglobin structure or synthesis and/or red cell enzyme deficiencies, etc), pyridoxine responsive anemia, or cirrhosis of the liver.

Cyanocobalamin is contraindicated in patients with sensitivity to cobalt or to cyanocobalamin (vitamin B-12)

WARNING

Accidental overdose of iron-containing products is a leading cause of fatal poisoning in children under 6. Keep this product out of the reach of children. In case of accidental overdose, call a doctor or a Poison Control Center immediately.

WARNING/PRECAUTIONS

Vitafol-Plus should be used with caution in patients with known sensitivity or allergy to soy.

Vitamin D supplementation should be used with caution in those with hypercalcemia or conditions that may lead to hypercalcemia such as hyperparathyroidism and those who form calcium-containing kidney stones. High doses of vitamin D can lead to elevated levels of calcium that reside in the blood and soft tissues. Bone pain, high blood pressure, formation of kidney stones, renal failure, and increased risk of heart disease can occur.

Iodine should be used with caution in patients with an overactive thyroid.

Prolonged use of iron salts may produce iron storage disease.

Folic acid, especially in doses above 0.1 mg daily, may obscure pernicious anemia, in that hematologic remission may occur while neurological manifestations remain progressive.

The use of folic acid doses above 1 mg daily may precipitate or exacerbate the neurological damage of vitamin B12 deficiency.

Consumption of more than 3 grams of omega-3 fatty acids per day from all sources may lead to excessive bleeding. Supplemental intake of omega-3 fatty acids such as DHA exceeding 2 grams per day is not recommended.

Avoid Overdosage. Keep out of the reach of children.

Drug Interactions

Medications for an overactive thyroid (anti-thyroid drugs) used in conjunction with iodine supplementation may lead to hypothyroidism.

Medications for hypertension used in conjunction with iodine supplementation may increase potassium.

High doses of folic acid may result in decreased serum levels of the anticonvulsant drugs carbamazepine, fosphenytoin, phenytoin, phenobarbitol, and valproic acid. Folic acid may decrease a patient's response to methotrexate.

Vitamin D supplementation should not be given with large amounts of calcium in those with hypercalcemia or conditions that may lead to hypercalcemia such as hyperparathyroidism and those who form calcium-containing kidney stones.

Zinc can inhibit the absorption of certain antibiotics; take at least 2 hours apart to minimize interactions.

Consult appropriate references for additional specific vitamin-drug interactions.

Information for Patients

Patients should be counseled to disclose all medical conditions, including pregnancy and breast-feeding, and the use of all medications and dietary supplements.

Pediatric Use

Not for Pediatric Use.

ADVERSE REACTIONS

Adverse reactions have been reported with specific vitamins and minerals, but generally at doses substantially higher than those in Vitafol®-Plus. However, allergic and idiosyncratic reactions are possible at any dose. Reported adverse events include skin ailments, gastrointestinal complaints, glucose abnormalities, and visual problems.

DOSAGE AND ADMINISTRATION

Before, during and after pregnancy, one softgel capsule daily, or as directed by a physician.

HOW SUPPLIED

STORAGE AND HANDLING

Vitafol®-Plus is available as a purple, oval shaped softgel capsule imprinted EV0092. Available in Box of Unit-Dose pack of 30 (5 child resistant blister cards of 6 softgel capsules) (NDC0642-0092-30), and as professional samples (NDC0642-0092-01). Store at room temperature, approximately 15°-30°C (59°-86°F). Avoid excessive heat, moisture and protect from light.

Rx only

Manufactured for
EVERETT LABORATORIES, INC.
West Orange, NJ 07052
1-877-324-9349

Patent Pending
Vitafol® is a trademark of Everett Laboratories, Inc.

life's DHA is a trademark of DSM.
U.S. Patent No. 5,492,938; 7,163,811

(Rev. 03/12)

PRINCIPAL DISPLAY PANEL - 30 Capsule Carton

NDC 0642-0092-30

Vitafol®-Plus
Prenatal Supplement with DHA

Small, All-In-One,
Once Daily Softgel Capsule

EV0092

Actual Size

DOES NOT CONTAIN
FISH OIL

life's DHA
HEALTHY BRAIN, EYES, HEART™

Unit Dose Pack
30 Softgel Capsules

Rx only
Patent Pending